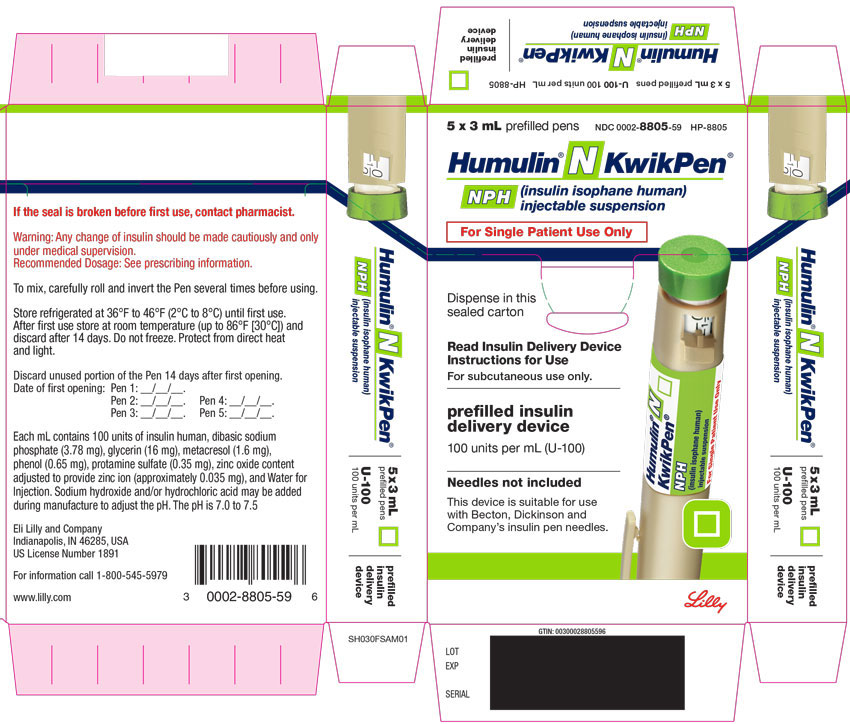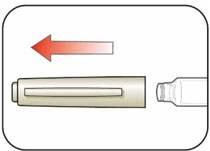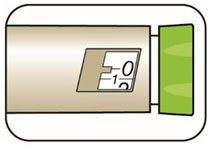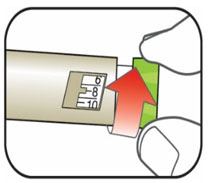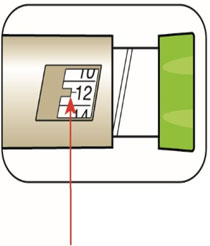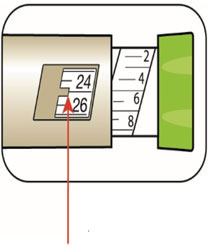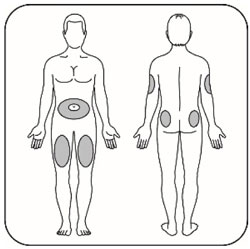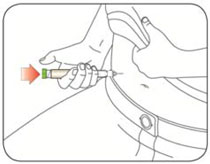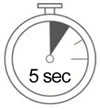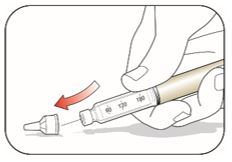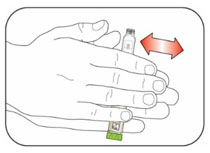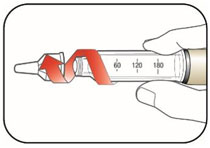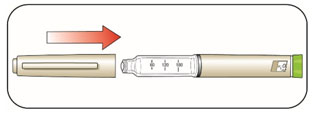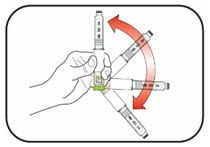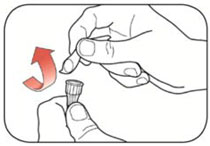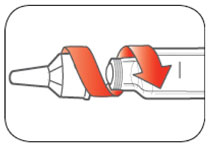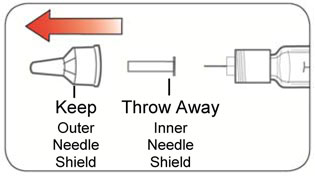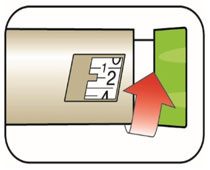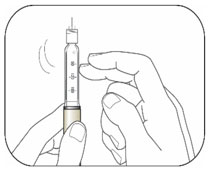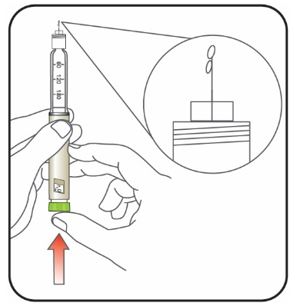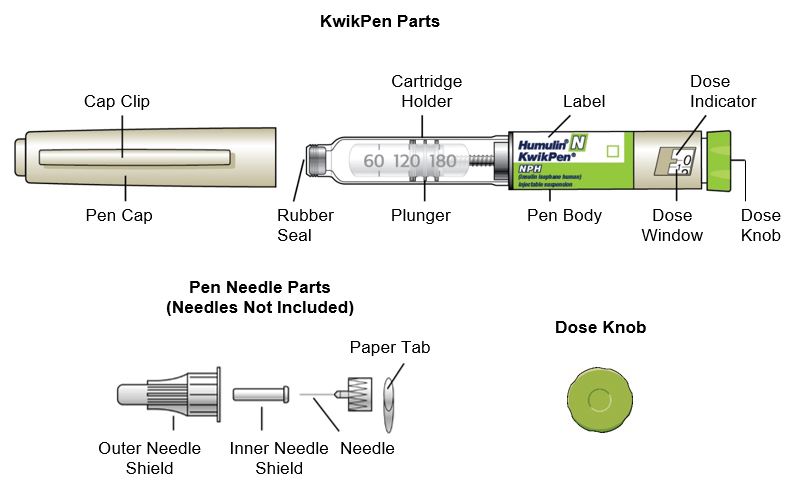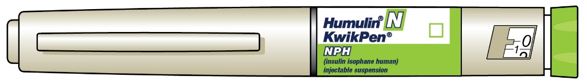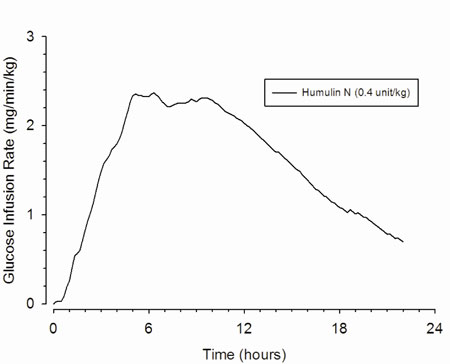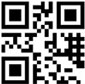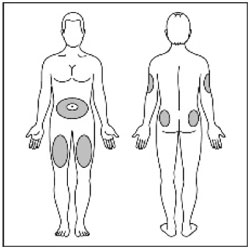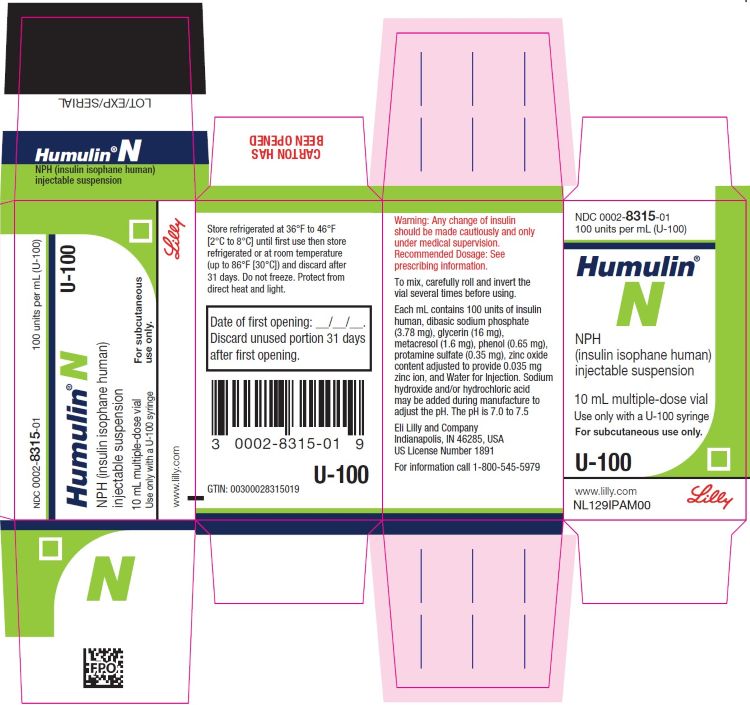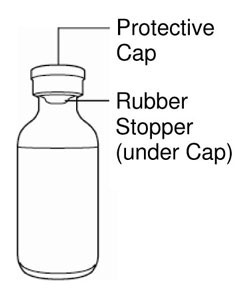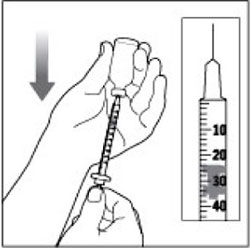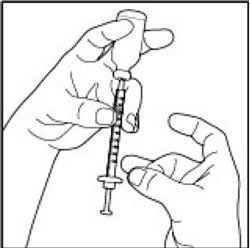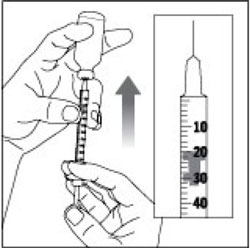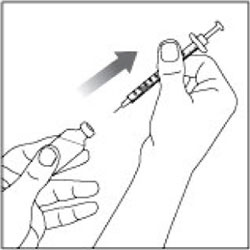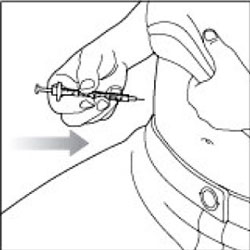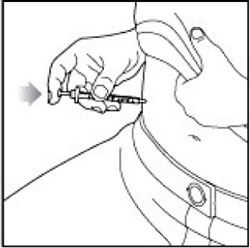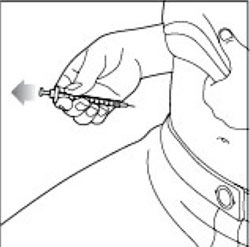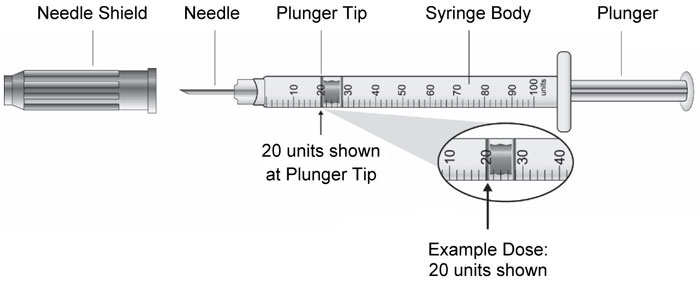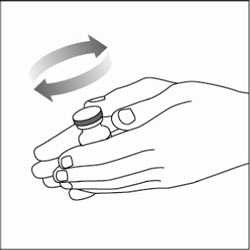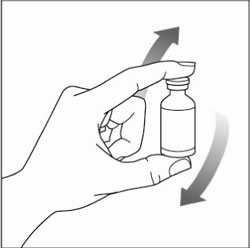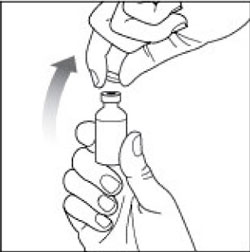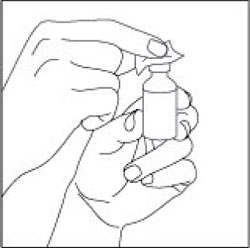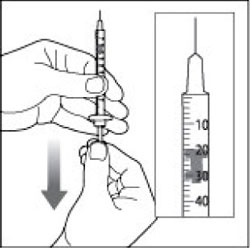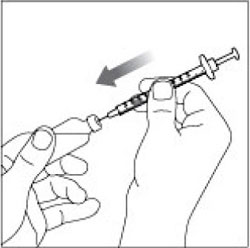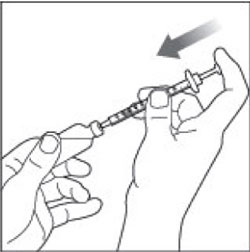 DRUG LABEL: Humulin 
NDC: 0002-8315 | Form: INJECTION, SUSPENSION
Manufacturer: Eli Lilly and Company
Category: otc | Type: HUMAN OTC DRUG LABEL
Date: 20251219

ACTIVE INGREDIENTS: Insulin human
 100 [iU]/1 mL
INACTIVE INGREDIENTS: Sodium phosphate, dibasic, unspecified form 3.78 mg/1 mL; Glycerin 16 mg/1 mL; Metacresol 1.6 mg/1 mL; Phenol 0.65 mg/1 mL; Protamine Sulfate 0.35 mg/1 mL; Zinc 0.035 mg/1 mL; Water; Hydrochloric acid; Sodium hydroxide

HIGHLIGHTS OF PRESCRIBING INFORMATION

These highlights do not include all the information needed to use HUMULIN N safely and effectively. See full prescribing information for HUMULIN N.
HUMULIN N (insulin isophane human) injectable suspension, for subcutaneous use
Initial U.S. Approval: 1982

1 INDICATIONS AND USAGE

HUMULIN® N is an intermediate-acting human insulin indicated to improve glycemic control in adult and pediatric patients with diabetes mellitus. (1)

2 DOSAGE AND ADMINISTRATION

- Only administer subcutaneously (in abdominal wall, thigh, upper arm, or buttocks). (2.2)
- Rotate injection sites to reduce risk of lipodystrophy and localized cutaneous amyloidosis. (2.2)
- Individualize and adjust dosage based on metabolic needs, blood glucose monitoring results and glycemic control goal. (2.3)
- See Full Prescribing Information for dosage adjustments due to drug interactions and patients with renal and hepatic impairment. (2.3, 2.4)
- May use with a meal-time insulin if indicated. (2.4)

3 DOSAGE FORMS AND STRENGTHS

Injectable suspension: 100 units/mL (U-100) available as:

- 10 mL multiple-dose vial (3)
- 3 mL single-patient-use HUMULIN® N KwikPen® prefilled pen (3)

4 CONTRAINDICATIONS

- During episodes of hypoglycemia. (4)
- In patients with hypersensitivity to HUMULIN N or any of its excipients. (4)

5 WARNINGS AND PRECAUTIONS

- Never share a HUMULIN N KwikPen or syringe between patients, even if the needle is changed. (5.1)
- Hyperglycemia or Hypoglycemia with Changes in Insulin Regimen: Make changes to a patient's insulin regimen (e.g., insulin strength, manufacturer, type, injection site or method of administration) under close medical supervision with increased frequency of blood glucose monitoring. (5.2)
- Hypoglycemia: May be life-threatening. Monitor blood glucose and increase monitoring frequency with changes to insulin dosage, use of glucose lowering medications, meal pattern, physical activity; in patients with renal or hepatic impairment; and in patients with hypoglycemia unawareness. (5.3, 7, 8.6, 8.7)
- Hypoglycemia Due to Medication Errors: Accidental mix-ups between insulin products can occur. Instruct patients to check insulin labels before injection. (5.4)
- Hypersensitivity Reactions: May be life-threatening. Discontinue HUMULIN N, monitor and treat if indicated. (5.5)
- Hypokalemia: May be life-threatening. Monitor potassium levels in patients at risk of hypokalemia and treat if indicated. (5.6)
- Fluid Retention and Heart Failure with Concomitant Use of Thiazolidinediones (TZDs): Observe for signs and symptoms of heart failure; consider dosage reduction or discontinuation if heart failure occurs. (5.7)

6 ADVERSE REACTIONS

Adverse reactions observed with HUMULIN N include hypoglycemia, allergic reactions, injection site reactions, lipodystrophy, pruritus, rash, weight gain, and edema. (6)

To report SUSPECTED ADVERSE REACTIONS, contact Eli Lilly and Company at 1-800-LillyRx (1-800-545-5979) or FDA at 1-800-FDA-1088 or www.fda.gov/medwatch.

7 DRUG INTERACTIONS

- Drugs that Affect Glucose Metabolism: Adjustment of insulin dosage may be needed. (7)
- Antiadrenergic Drugs (e.g., beta-blockers, clonidine, guanethidine, and reserpine): Signs and symptoms of hypoglycemia may be reduced or absent. (5.3, 7)

FULL PRESCRIBING INFORMATION

1 INDICATIONS AND USAGE

HUMULIN N is indicated to improve glycemic control in adults and pediatric patients with diabetes mellitus.

2 DOSAGE AND ADMINISTRATION

2.1 Important Administration Instructions

Inspect HUMULIN N visually before use. It should not contain particulate matter and should appear uniformly cloudy after mixing. Do not use HUMULIN N if particulate matter is seen.

Use HUMULIN N KwikPen with caution in patients with visual impairment that may rely on audible clicks to dial their dose.

2.2 Route of Administration

HUMULIN N should only be administered subcutaneously.

Administer in the subcutaneous tissue of the abdominal wall, thigh, upper arm, or buttocks. Rotate injection sites within the same region from one injection to the next to reduce the risk of lipodystrophy and localized cutaneous amyloidosis. Do not inject into areas of lipodystrophy or localized cutaneous amyloidosis [see Warnings and Precautions (5.2) and Adverse Reactions (6)]. During changes to a patient's insulin regimen, increase the frequency of blood glucose monitoring [see Warnings and Precautions (5.2)].

The HUMULIN N KwikPen dials in 1 unit increments.

Do not administer HUMULIN N intravenously and do not use HUMULIN N in an insulin infusion pump.

2.3 Dosage Information

Individualize and adjust the dosage of HUMULIN N based on the individual's metabolic needs, blood glucose monitoring results and glycemic control goal.

Dosage adjustments may be needed with changes in physical activity, changes in meal patterns (i.e., macronutrient content or timing of food intake), changes in renal or hepatic function or during acute illness [see Warnings and Precautions (5.2, 5.3), and Use in Specific Populations (8.6, 8.7)].

2.4 Dosage Adjustment due to Drug Interactions

Dosage adjustment may be needed when HUMULIN N is coadministered with certain drugs [see Drug Interactions (7)].

Dosage adjustment may be needed when changing from another insulin to HUMULIN N [see Warnings and Precautions (5.2)].

Instructions for Mixing with Other Insulins

HUMULIN N may be used with a prandial insulin if indicated. HUMULIN N may be mixed with HUMULIN R or HUMALOG before injection.

- If HUMULIN N is mixed with HUMULIN R, HUMULIN R should be drawn into the syringe first. Injection should occur immediately after mixing.
- If HUMULIN N is mixed with HUMALOG, HUMALOG should be drawn into the syringe first. Injection should occur immediately after mixing.

3 DOSAGE FORMS AND STRENGTHS

Injectable suspension: 100 units/mL (U-100) white and cloudy suspension available as:

- 10 mL multiple-dose vial
- 3 mL single-patient-use HUMULIN N KwikPen prefilled pen

4 CONTRAINDICATIONS

HUMULIN N is contraindicated:

- During episodes of hypoglycemia [see Warnings and Precautions (5.3)], and
- In patients who have had hypersensitivity reactions to HUMULIN N or any of its excipients [see Warnings and Precautions (5.5)].

5 WARNINGS AND PRECAUTIONS

5.1 Never Share a HUMULIN N KwikPen or Syringe Between Patients

HUMULIN N KwikPens must never be shared between patients, even if the needle is changed. Patients using HUMULIN N vials must never share needles or syringes with another person. Sharing poses a risk for transmission of blood-borne pathogens.

5.2 Hyperglycemia or Hypoglycemia with Changes in Insulin Regimen

Changes in an insulin regimen (e.g., insulin strength, manufacturer, type, injection site or method of administration) may affect glycemic control and predispose to hypoglycemia [see Warnings and Precautions (5.3)] or hyperglycemia. Repeated insulin injections into areas of lipodystrophy or localized cutaneous amyloidosis have been reported to result in hyperglycemia; and a sudden change in the injection site (to an unaffected area) has been reported to result in hypoglycemia [see Adverse Reactions (6)].

Make any changes to a patient's insulin regimen under close medical supervision with increased frequency of blood glucose monitoring. Advise patients who have repeatedly injected into areas of lipodystrophy or localized cutaneous amyloidosis to change the injection site to unaffected areas and closely monitor for hypoglycemia. For patients with type 2 diabetes, dosage adjustments of concomitant antidiabetic products may be needed.

5.3 Hypoglycemia

Hypoglycemia is the most common adverse reaction associated with insulins, including HUMULIN N. Severe hypoglycemia can cause seizures, may be life-threatening or cause death. Hypoglycemia can impair concentration ability and reaction time; this may place the patient and others at risk in situations where these abilities are important (e.g., driving or operating other machinery).

Hypoglycemia can happen suddenly and symptoms may differ in each patient and change over time in the same patient. Symptomatic awareness of hypoglycemia may be less pronounced in patients with longstanding diabetes, in patients with diabetic neuropathy, in patients using medications that block the sympathetic nervous system (e.g., beta-blockers) [see Drug Interactions (7)], or in patients who experience recurrent hypoglycemia.

Risk Factors for Hypoglycemia

The risk of hypoglycemia after an injection is related to the duration of action of the insulin and, in general, is highest when the glucose lowering effect of the insulin is maximal. As with all insulins, the glucose lowering effect time course of HUMULIN N may vary in different individuals or at different times in the same individual and depends on many conditions, including the area of injection as well as the injection site blood supply and temperature [see Clinical Pharmacology (12.2)].

Other factors which may increase the risk of hypoglycemia include changes in meal pattern (e.g., macronutrient content or timing of meals), changes in level of physical activity, or changes to concomitant drugs [see Drug Interactions (7)]. Patients with renal or hepatic impairment may be at higher risk of hypoglycemia [see Use in Specific Populations (8.6, 8.7)].

Risk Mitigation Strategies for Hypoglycemia

Patients and caregivers must be educated to recognize and manage hypoglycemia. Self-monitoring of blood glucose plays an essential role in the prevention and management of hypoglycemia. In patients at higher risk for hypoglycemia and patients who have reduced symptomatic awareness of hypoglycemia, increased frequency of blood glucose monitoring is recommended.

5.4 Hypoglycemia Due to Medication Errors

Accidental mix-ups between insulin products have been reported. To avoid medication errors between HUMULIN N and other insulins, instruct patients to always check the insulin label before each injection.

5.5 Hypersensitivity Reactions

Severe, life-threatening, generalized allergy, including anaphylaxis, can occur with insulins, including HUMULIN N. If hypersensitivity reactions occur, discontinue HUMULIN N; treat per standard of care and monitor until symptoms and signs resolve [see Adverse Reactions (6)]. HUMULIN N is contraindicated in patients who have had hypersensitivity reactions to HUMULIN N or any of its excipients.

5.6 Hypokalemia

All insulins, including HUMULIN N, cause a shift in potassium from the extracellular to intracellular space, possibly leading to hypokalemia. Untreated hypokalemia may cause respiratory paralysis, ventricular arrhythmia, and death. Monitor potassium levels in patients at risk for hypokalemia if indicated (e.g., patients using potassium-lowering medications, patients taking medications sensitive to serum potassium concentrations).

5.7 Fluid Retention and Heart Failure with Concomitant Use of PPAR-gamma Agonists

Thiazolidinediones (TZDs), which are peroxisome proliferator-activated receptor (PPAR)-gamma agonists, can cause dose-related fluid retention, when used in combination with insulin. Fluid retention may lead to or exacerbate heart failure. Patients treated with insulin, including HUMULIN N, and a PPAR-gamma agonist should be observed for signs and symptoms of heart failure. If heart failure develops, it should be managed according to current standards of care, and discontinuation or dose reduction of the PPAR-gamma agonist must be considered.

6 ADVERSE REACTIONS

The following adverse reactions are discussed elsewhere in the labeling:

- Hypoglycemia [see Warnings and Precautions (5.3)].
- Hypoglycemia Due to Medication Errors [see Warnings and Precautions (5.4)].
- Hypersensitivity Reactions [see Warnings and Precautions (5.5)]
- Hypokalemia [see Warnings and Precautions (5.6)].

The following additional adverse reactions have been identified during post-approval use of HUMULIN N. Because these reactions are reported voluntarily from a population of uncertain size, it is not always possible to reliably estimate their frequency or to establish a causal relationship to drug exposure.

Allergic Reactions

Some patients taking HUMULIN N have experienced erythema, local edema, and pruritus at the site of injection. These conditions were usually self-limiting. Severe cases of generalized allergy (anaphylaxis) have been reported [see Warnings and Precautions (5.5)].

Peripheral Edema

Some patients taking HUMULIN N have experienced sodium retention and edema, particularly if previously poor metabolic control is improved by intensified insulin therapy.

Lipodystrophy

Administration of insulin subcutaneously, including HUMULIN N, has resulted in lipoatrophy (depression in the skin) or lipohypertrophy (enlargement or thickening of tissue) [see Dosage and Administration (2.2)] in some patients.

Localized Cutaneous Amyloidosis

Localized cutaneous amyloidosis at the injection site has occurred. Hyperglycemia has been reported with repeated insulin injections into areas of localized cutaneous amyloidosis; hypoglycemia has been reported with a sudden change to an unaffected injection site.

Weight gain

Weight gain has occurred with insulins, including HUMULIN N, and has been attributed to the anabolic effects of insulin and the decrease in glycosuria.

Immunogenicity

Development of antibodies that react with human insulin have been observed with all insulins, including HUMULIN N.

7 DRUG INTERACTIONS

Table 1: Clinically Significant Drug Interactions with HUMULIN N
Drugs that May Increase the Risk of Hypoglycemia
Drugs: | Antidiabetic agents, ACE inhibitors, angiotensin II receptor blocking agents, disopyramide, fibrates, fluoxetine, monoamine oxidase inhibitors, pentoxifylline, pramlintide, salicylates, somatostatin analog (e.g., octreotide), and sulfonamide antibiotics
Intervention: | Dose adjustment and increased frequency of glucose monitoring may be required when HUMULIN N is co-administered with these drugs.
Drugs that May Decrease the Blood Glucose Lowering Effect of HUMULIN N
Drugs: | Atypical antipsychotics (e.g., olanzapine and clozapine), corticosteroids, danazol, diuretics, estrogens, glucagon, isoniazid, niacin, oral contraceptives, phenothiazines, progestogens (e.g., in oral contraceptives), protease inhibitors, somatropin, sympathomimetic agents (e.g., albuterol, epinephrine, terbutaline), and thyroid hormones.
Intervention: | Dose adjustment and increased frequency of glucose monitoring may be required when HUMULIN N is co-administered with these drugs.
Drugs that May Increase or Decrease the Blood Glucose Lowering Effect of HUMULIN N
Drugs: | Alcohol, beta-blockers, clonidine, and lithium salts. Pentamidine may cause hypoglycemia, which may sometimes be followed by hyperglycemia.
Intervention: | Dose adjustment and increased frequency of glucose monitoring may be required when HUMULIN N is co-administered with these drugs.
Drugs that May Blunt Signs and Symptoms of Hypoglycemia
Drugs: | Beta-blockers, clonidine, guanethidine, and reserpine
Intervention: | Increased frequency of glucose monitoring may be required when HUMULIN N is co-administered with these drugs.

8 USE IN SPECIFIC POPULATIONS

8.1 Pregnancy

Risk Summary

Available data from published studies over decades have not established an association with human insulin use during pregnancy and major birth defects, miscarriage, or adverse maternal or fetal outcomes (see Data). There are risks to the mother and fetus associated with poorly controlled diabetes in pregnancy (see Clinical Considerations). Animal reproduction studies were not performed.

The estimated background risk of major birth defects is 6-10% in women with pre-gestational diabetes with a HbA1c >7% and has been reported to be as high as 20-25% in women with a HbA1c >10%. The estimated background risk of miscarriage for the indicated population is unknown. In the U.S. general population, the estimated background risk of major birth defects and miscarriage in clinically recognized pregnancies is 2-4% and 15-20%, respectively.

Clinical Considerations

Disease-associated maternal and/or embryo/fetal risk

Poorly controlled diabetes in pregnancy increases the maternal risk for diabetic ketoacidosis, pre-eclampsia, spontaneous abortions, preterm delivery, and delivery complications. Poorly controlled diabetes increases the fetal risk for major birth defects, stillbirth, and macrosomia-related morbidity.

Data

Human Data

While available studies cannot definitively establish the absence of risk, published data from retrospective studies, open-label, randomized, parallel studies and meta-analyses over decades have not established an association with human insulin use during pregnancy and major birth defects, miscarriage, or adverse maternal or fetal outcomes. All available studies have methodological limitations, including lack of blinding, unclear methods or randomization, and small sample size.

8.2 Lactation

Risk Summary

Available data from published literature suggests that exogenous human insulin products, including HUMULIN N, are transferred into human milk. There are no adverse reactions reported in breastfed infants in the literature. There are no data on the effects of exogenous human insulin products, including HUMULIN N on milk production. The developmental and health benefits of breastfeeding should be considered along with the mother's clinical need for HUMULIN N and any potential adverse effects on the breastfed child from HUMULIN N or from the underlying maternal condition.

8.4 Pediatric Use

HUMULIN N is indicated to improve glycemic control in pediatric patients with diabetes mellitus.

8.5 Geriatric Use

The effect of age on the pharmacokinetics and pharmacodynamics of HUMULIN N has not been studied [see Clinical Pharmacology (12.3)]. Patients with advanced age using any insulin, including HUMULIN N, may be at increased risk of hypoglycemia due to co-morbid disease and polypharmacy [see Warnings and Precautions (5.3)].

8.6 Renal Impairment

The effect of renal impairment on the pharmacokinetics and pharmacodynamics of HUMULIN N has not been studied [see Clinical Pharmacology (12.3)]. Patients with renal impairment are at increased risk of hypoglycemia and may require more frequent HUMULIN N dose adjustment and more frequent blood glucose monitoring.

8.7 Hepatic Impairment

The effect of hepatic impairment on the pharmacokinetics and pharmacodynamics of HUMULIN N has not been studied [see Clinical Pharmacology (12.3)]. Patients with hepatic impairment are at increased risk of hypoglycemia and may require more frequent HUMULIN N dose adjustment and more frequent blood glucose monitoring.

10 OVERDOSAGE

Excess insulin administration may cause hypoglycemia and hypokalemia [see Warnings and Precautions (5.3, 5.6)]. Mild episodes of hypoglycemia can be treated with oral glucose. Adjustments in drug dosage, meal patterns, or physical activity level may be needed. More severe episodes with coma, seizure, or neurologic impairment may be treated with a glucagon product for emergency use or concentrated intravenous glucose. Sustained carbohydrate intake and observation may be necessary because hypoglycemia may recur after apparent clinical recovery. Hypokalemia must be corrected appropriately.

11 DESCRIPTION

Insulin isophane human is produced by recombinant DNA technology utilizing a non-pathogenic laboratory strain of Escherichia coli. Insulin isophane human is a suspension of crystals produced from combining human insulin and protamine sulfate under appropriate conditions for crystal formation. The amino acid sequence of insulin isophane human is identical to human insulin and has the empirical formula C257H383N65O77S6 with a molecular weight of 5.808 kDa.

HUMULIN N (insulin isophane human) injectable suspension is an intermediate acting human insulin. It is a sterile, white and cloudy suspension that contains insulin isophane human suspension (NPH) for subcutaneous use. Each milliliter of HUMULIN N contains 100 units of insulin human, dibasic sodium phosphate (3.78 mg), glycerin (16 mg), metacresol (1.6 mg), phenol (0.65 mg), protamine sulfate (0.35 mg), zinc oxide content adjusted to provide 0.035 mg zinc ion, and Water for Injection. The pH is 7.0 to 7.5. Sodium hydroxide and/or hydrochloric acid may be added during manufacture to adjust the pH.

12 CLINICAL PHARMACOLOGY

12.1 Mechanism of Action

HUMULIN N lowers blood glucose by stimulating peripheral glucose uptake by skeletal muscle and fat, and by inhibiting hepatic glucose production. Insulins inhibit lipolysis and proteolysis, and enhance protein synthesis.

12.2 Pharmacodynamics

HUMULIN N is an intermediate-acting insulin with a slower onset of action and a longer duration of activity than that of regular human insulin. In a study in which healthy subjects (n=16) received subcutaneous injections of HUMULIN N (0.4 unit/kg) on 4 occasions, the median maximum effect occurred at 6.5 hours (range: 2.8 to 13 hours). In this study, insulin activity was measured by the rate of glucose infusions.

The time course of action of insulin, such as HUMULIN N may vary in different individuals or within the same individual. The parameters of HUMULIN N activity (time of onset, peak time, and duration) as designated in Figure 1 should be considered only as general guidelines. The rate of insulin absorption and consequently the onset of activity is known to be affected by the site of injection, physical activity level, and other variables [see Warnings and Precautions (5.3)].

Figure 1: Mean Insulin Activity Versus Time Profile After Subcutaneous Injection of HUMULIN N (0.4 unit/kg) in Healthy Subjects.

12.3 Pharmacokinetics

Absorption — In healthy subjects given subcutaneous doses of HUMULIN N (0.4 unit/kg), median peak serum concentration of insulin occurred at approximately 4 hours (range: 1 to 12 hours) after dosing.

Metabolism — The uptake and degradation of insulin occurs predominantly in liver, kidney, muscle, and adipocytes, with the liver being the major organ involved in the clearance of insulin.

Elimination — Because of the absorption-rate limited kinetics of insulin mixtures, a true half-life cannot be accurately estimated from the terminal slope of the concentration versus time curve. In healthy subjects given subcutaneous doses of HUMULIN N (0.4 unit/kg), the mean apparent half-life was approximately 4.4 hours (range: 1-84 hours).

Specific Populations

The effects of age, gender, race, obesity, pregnancy, or smoking on the pharmacokinetics of HUMULIN N have not been studied.

13 NONCLINICAL TOXICOLOGY

13.1 Carcinogenesis, Mutagenesis, Impairment of Fertility

Carcinogenicity and fertility studies were not performed in animals. Biosynthetic human insulin was not genotoxic in the in vivo sister chromatid exchange assay and the in vitro gradient plate and unscheduled DNA synthesis assays.

16 HOW SUPPLIED/STORAGE AND HANDLING

16.1 How Supplied

HUMULIN N (insulin isophane human) injectable suspension, 100 units/mL (U-100), is a white and cloudy suspension available as:

10 mL multiple-dose vial | NDC 0002-8315-01 (HI-310)
5 x 3 mL single-patient-use HUMULIN N KwikPen | NDC 0002-8805-59 (HP-8805)

Each prefilled HUMULIN N KwikPen is for use by a single patient. HUMULIN N KwikPens must never be shared between patients, even if the needle is changed. Patients using HUMULIN N vials must never share needles or syringes with another person.

The HUMULIN N KwikPen dials in 1 unit increments.

16.2 Storage and Handling

Dispense in the original sealed carton with the enclosed Instructions for Use.

Protect from heat and light. Do not freeze. Do not use if it has been frozen. See Table 2 below for storage conditions.

Table 2: Storage Conditions for HUMULIN N Vials and Pens
 | Not In-use (Unopened) |  | In-use (Opened)
 | Room Temperature (up to 86°F [30°C]) | Refrigerated (36° to 46°F [2° to 8°C]) | Room Temperature (up to 86°F [30°C]) | Refrigerated (36° to 46°F [2° to 8°C])
10 mL multiple-dose viala | 31 days | Until expiration date | 31 days | 31 days
3 mL single-patient-use HUMULIN N KwikPenb | 14 days | Until expiration date | 14 days | Do not refrigerate.
a When stored at room temperature, HUMULIN N vial can only be used for a total of 31 days including both not in-use (unopened) and in-use (opened) storage time.
b When stored at room temperature, HUMULIN N KwikPen can only be used for a total of 14 days including both not in-use (unopened) and in-use (opened) storage time.

17 PATIENT COUNSELING INFORMATION

Advise the patient to read the FDA-approved patient labeling (Patient Information and Instructions for Use).

Never Share a HUMULIN N KwikPen or Syringe Between Patients

Advise patients that they must never share a HUMULIN N KwikPen with another person, even if the needle is changed. Advise patients using HUMULIN N vials not to share needles or syringes with another person. Sharing poses a risk for transmission of blood-borne pathogens [see Warnings and Precautions (5.1)].

Hyperglycemia or Hypoglycemia

Instruct patients on self-management procedures including glucose monitoring, proper injection technique, and management of hypoglycemia and hyperglycemia especially at initiation of HUMULIN N therapy. Instruct patients on handling of special situations such as intercurrent conditions (illness, stress, or emotional disturbances), an inadequate or skipped insulin dose, inadvertent administration of an increased insulin dose, inadequate food intake, and skipped meals. Instruct patients on the management of hypoglycemia.

Inform patients that their ability to concentrate and react may be impaired as a result of hypoglycemia. Advise patients who have frequent hypoglycemia or reduced or absent warning signs of hypoglycemia to use caution when driving or operating machinery [see Warnings and Precautions (5.3)].

Advise patients that changes in insulin regimen can predispose to hyperglycemia or hypoglycemia and that changes in insulin regimen should be made under close medical supervision [see Warnings and Precautions (5.2)].

Inform patients that accidental mix-ups between insulin products have been reported. Instruct patients to always carefully check that they are administering the correct insulin (e.g., by checking the insulin label before each injection) to avoid medication errors between HUMULIN N and other insulins.

Hypersensitivity Reactions

Advise patients that hypersensitivity reactions have occurred with HUMULIN N. Inform patients on the symptoms of hypersensitivity reactions [see Warnings and Precautions (5.5)].

____________

HUMULIN® and HUMULIN® N KwikPen® are trademarks of Eli Lilly and Company.

Literature revised December 2025

Manufactured by:
Eli Lilly and Company
Indianapolis, IN 46285, USA
US License Number 1891
Copyright © 1997, 2025, Eli Lilly and Company. All rights reserved.

LINN-0008-USPI-20251219

PATIENT INFORMATION

HUMULIN® (HU-mu-lin) N
(insulin isophane human)
injectable suspension, for subcutaneous use

Do not share your HUMULIN N KwikPen or syringes with other people, even if the needle has been changed. You may give other people a serious infection or get a serious infection from them.

What is HUMULIN N?

- HUMULIN N is a man-made insulin that is used to control high blood sugar in adults and children with diabetes mellitus.

Who should not use HUMULIN N?

Do not use HUMULIN N if you:

- are having an episode of low blood sugar (hypoglycemia).
- have an allergy to HUMULIN N or any of the ingredients in HUMULIN N.

Before using HUMULIN N, tell your healthcare provider about all your medical conditions including, if you:

- have liver or kidney problems.
- take any other medicines, especially ones commonly called TZDs (thiazolidinediones).
- have heart failure or other heart problems. If you have heart failure, it may get worse while you take TZDs with HUMULIN N.
- are pregnant, planning to become pregnant. Talk with your healthcare provider about the best way to control your blood sugar if you plan to become pregnant or while you are pregnant.
- are breast-feeding or plan to breastfeed. HUMULIN N may pass into your breast milk. Talk with your healthcare provider about the best way to feed your baby while using HUMULIN N.
- are taking new prescription or over-the-counter medicines, vitamins, or herbal supplements.

Before you start using HUMULIN N, talk to your healthcare provider about low blood sugar and how to manage it.

How should I use HUMULIN N?

- Read the Instructions for Use that come with your HUMULIN N.
- Use HUMULIN N exactly as your healthcare provider tells you to. HUMULIN N is injected under the skin (subcutaneously) of your stomach area, buttocks, upper legs or upper arms. Change (rotate) your injection sites within the area you choose with each dose to reduce your risk of getting lipodystrophy (pits in skin or thickened skin) and localized cutaneous amyloidosis (skin with lumps) at the injection sites. Do not use the exact same spot for each injection. Do not inject where the skin has pits, is thickened, or has lumps. Do not inject where the skin is tender, bruised, scaly or hard, or into scars or damaged skin.
- Know the type and strength of insulin you use. Do not change the type of insulin you use unless your healthcare provider tells you to. The amount of insulin and the best time for you to take your insulin may need to change if you use different types of insulin.
- Check your blood sugar levels. Ask your healthcare provider what your blood sugars should be and when you should check your blood sugar levels.
- Do not share your HUMULIN N KwikPen or syringes with other people, even if the needle has been changed. You may give other people a serious infection or get a serious infection from them.

Your HUMULIN N dose may need to change because of:

- change in level of physical activity or exercise, weight gain or loss, increased stress, illness, change in diet.

What should I avoid while using HUMULIN N?

While using HUMULIN N do not:

- drive or operate heavy machinery, until you know how HUMULIN N affects you.
- drink alcohol or use prescription or over-the-counter medicines that contain alcohol.

What are the possible side effects of HUMULIN N?

HUMULIN N may cause serious side effects that can lead to death, including:

- low blood sugar (hypoglycemia). Signs and symptoms that may indicate low blood sugar include:
  - dizziness or light-headedness, sweating, confusion, headache, blurred vision, slurred speech, shakiness, fast heartbeat, anxiety, irritability, or mood changes, hunger.
- serious allergic reaction (whole body reaction). Get medical help right away, if you have any of these symptoms of an allergic reaction:
  - a rash over your whole body, trouble breathing, a fast heartbeat, or sweating.
- low potassium in your blood (hypokalemia).
- heart failure. Taking certain diabetes pills called thiazolidinediones or “TZDs” with HUMULIN N may cause heart failure in some people. This can happen even if you have never had heart failure or heart problems before. If you already have heart failure it may get worse while you take TZDs with HUMULIN N. Your healthcare provider should monitor you closely while you are taking TZDs with HUMULIN N. Tell your healthcare provider if you have any new or worse symptoms of heart failure including:
- shortness of breath, swelling of your ankles or feet, sudden weight gain.
  Treatment with TZDs and HUMULIN N may need to be adjusted or stopped by your healthcare provider if you have new or worse heart failure.

Get emergency medical help if you have:

- trouble breathing, shortness of breath, fast heartbeat, swelling of your face, tongue, or throat, sweating, extreme drowsiness, dizziness, confusion.

The most common side effects of HUMULIN N include:

- low blood sugar (hypoglycemia), allergic reactions including reactions at the injection site, skin thickening or pits at the injection site (lipodystrophy), itching, rash, weight gain, and swelling of your hands and feet.

These are not all the possible side effects of HUMULIN N. Call your doctor for medical advice about side effects. You may report side effects to FDA at 1-800-FDA-1088.

General information about the safe and effective use of HUMULIN N:

Medicines are sometimes prescribed for purposes other than those listed in a Patient Information leaflet. You can ask your pharmacist or healthcare provider for information about HUMULIN N that is written for health professionals. Do not use HUMULIN N for a condition for which it was not prescribed. Do not give HUMULIN N to other people, even if they have the same symptoms that you have. It may harm them.

What are the ingredients in HUMULIN N?

Active Ingredient: insulin human

Inactive Ingredients: dibasic sodium phosphate, glycerin, metacresol, phenol, protamine sulfate, zinc oxide, and Water for Injection as inactive ingredients. Sodium hydroxide and/or hydrochloric acid may be added to adjust the pH.

For more information, call 1-800-545-5979 or go to www.humulin.com.

This Patient Information has been approved by the U.S. Food and Drug Administration.

Patient Information revised June 2022

Manufactured by:
Eli Lilly and Company, Indianapolis, IN 46285, USA
US License Number 1891
Copyright © 1997, 2022, Eli Lilly and Company. All rights reserved.

LINN-0005-PPI-20220627

VIAL INSTRUCTIONS FOR USE

Instructions for Use
HUMULIN® (HU-mu-lin) N
(insulin isophane human)
injectable suspension, for subcutaneous use
10 mL multiple-dose vial (100 units/mL)

Read the Instructions for Use before you start taking HUMULIN N and each time you get a new HUMULIN N vial. There may be new information. This information does not take the place of talking to your healthcare provider about your medical condition or your treatment.

Do not share your syringes with other people, even if the needle has been changed. You may give other people a serious infection or get a serious infection from them.

Supplies needed to give your injection:

- a 10 mL multiple-dose HUMULIN N vial
- a U-100 insulin syringe and needle
- 2 alcohol swabs
- 1 sharps container for throwing away used needles and syringes. See “Disposing of used needles and syringes” at the end of these instructions.

Vial

Syringe

Preparing your HUMULIN N dose:

- Wash your hands with soap and water.
- Check the HUMULIN N label to make sure you are taking the right type of insulin. This is especially important if you use more than 1 type of insulin.
- Do not use HUMULIN N past the expiration date printed on the label or 31 days after you first use it.
- Always use a new syringe or needle for each injection to help ensure sterility and prevent blocked needles. Do not reuse or share your syringes or needles with other people. You may give other people a serious infection or get a serious infection from them.

Step 1:
Gently roll the vial between the palms of your hands at least 10 times.

Step 2:
Carefully invert the vial at least 10 times.
Mixing is important to make sure you get the right dose. Humulin N should look white and cloudy after mixing. Do not use it if it looks clear or contains any lumps or particles.

Step 3:
If you are using a new vial, pull off the plastic Protective Cap, but do not remove the Rubber Stopper.

Step 4:
Wipe the Rubber Stopper with an alcohol swab.

Step 5:
Hold the syringe with the needle pointing up. Pull down on the Plunger until the tip of the Plunger reaches the line for the number of units for your prescribed dose.

(Example Dose: 20 units shown)

Step 6:
Push the needle through the Rubber Stopper of the vial.

Step 7:
Push the plunger all the way in. This puts air into the vial.

Step 8:
Turn the vial and syringe upside down and slowly pull the Plunger down until the tip is a few units past the line for your prescribed dose.
If there are air bubbles, tap the syringe gently a few times to let any air bubbles rise to the top.

(Example Dose: 20 units Plunger is shown at 24 units)

Step 9:
Slowly push the Plunger up until the tip reaches the line for your prescribed dose.
Check the syringe to make sure that you have the right dose.

(Example Dose: 20 units shown)

Step 10:
Pull the syringe out of the vial's Rubber Stopper.

Giving your HUMULIN N injection:

- Inject your insulin exactly as your healthcare provider has shown you.
- Change (rotate) your injection sites within the area you choose for each dose to reduce your risk of getting lipodystrophy (pits in skin or thickened skin) and localized cutaneous amyloidosis (skin with lumps) at the injection sites. Do not inject where the skin has pits, is thickened, or has lumps. Do not inject where the skin is tender, bruised, scaly or hard, or into scars or damaged skin.

Step 11:
Choose your injection site.
HUMULIN N is injected under the skin (subcutaneously) of your stomach area (abdomen), buttocks, upper legs or upper arms.
Wipe the skin with an alcohol swab. Let the injection site dry before you inject your dose.

Step 12:
Insert the needle into your skin.

Step 13:
Push down on the Plunger to inject your dose.
The needle should stay in your skin for at least 5 seconds to make sure you have injected all of your insulin dose.

Step 14:
Pull the needle out of your skin.

- If you see blood after you take the needle out of your skin, press the injection site with a piece of gauze or an alcohol swab. Do not rub the area.
- Do not recap the needle. Recapping the needle can lead to a needle stick injury.

Disposing of used needles and syringes:

- Put your used needles and syringes in a FDA-cleared sharps disposal container right away after use. Do not throw away (dispose of) loose needles and syringes in your household trash.
- If you do not have a FDA-cleared sharps disposal container, you may use a household container that is:
  - made of a heavy-duty plastic,
  - can be closed with a tight-fitting, puncture-resistant lid, without sharps being able to come out,
  - upright and stable during use,
  - leak-resistant, and
  - properly labeled to warn of hazardous waste inside the container.
- When your sharps disposal container is almost full, you will need to follow your community guidelines for the right way to dispose of your sharps disposal container. There may be state or local laws about how you should throw away used needles and syringes. For more information about safe sharps disposal, and for specific information about sharps disposal in the state that you live in, go to the FDA's website at: http://www.fda.gov/safesharpsdisposal
- Do not dispose of your used sharps disposal container in your household trash unless your community guidelines permit this. Do not recycle your used sharps disposal container.

How should I store HUMULIN N?

All unopened HUMULIN N vials:

- Store all unopened vials in the refrigerator.
- Do not freeze. Do not use if it has been frozen.
- Keep away from heat and out of direct light.
- Unopened vials can be used until the expiration date on the carton and label, if they have been stored in the refrigerator.
- Unopened vials should be thrown away after 31 days, if they are stored at room temperature.

After HUMULIN N vials have been opened:

- Store opened vials in the refrigerator or at room temperature up to 86°F (30°C) for up to 31 days.
- Keep away from heat and out of direct light.
- Throw away all opened vials after 31 days of use, even if there is still insulin left in the vial.

General information about the safe and effective use of HUMULIN N.

- Keep HUMULIN N vials, syringes, needles, and all medicines out of the reach of children.
- Always use a new syringe or needle for each injection.
- Do not reuse or share your syringes or needles with other people. You may give other people a serious infection or get a serious infection from them.

If you have any questions or problems with your HUMULIN, contact Lilly at 1-800-Lilly-Rx (1-800-545-5979) or call your healthcare provider for help. For more information on HUMULIN and insulin, go to www.humulin.com.

Scan this code to launch the humulin.com website

This Instructions for Use has been approved by the U.S. Food and Drug Administration.

Humulin® is a trademark of Eli Lilly and Company.

Instructions for Use revised: November 2025

Manufactured by:
Eli Lilly and Company, Indianapolis, IN 46285, USA
US License Number 1891
Copyright © 1992, 2025, Eli Lilly and Company. All rights reserved.

LINNVL-0006-IFU-20251119

KWIKPEN INSTRUCTIONS FOR USE

Instructions for Use

HUMULIN® N KwikPen®

(insulin isophane human)
injectable suspension, for subcutaneous use
3 mL single-patient-use pen (100 units/mL)

Read the Instructions for Use before you start taking HUMULIN N and each time you get another KwikPen. There may be new information. This information does not take the place of talking to your healthcare provider about your medical condition or your treatment.

Do not share your HUMULIN N KwikPen with other people, even if the needle has been changed. You may give other people a serious infection or get a serious infection from them.

HUMULIN® N KwikPen® (“Pen”) is a disposable single-patient-use prefilled pen containing 300 units of HUMULIN N. You can give yourself more than 1 dose from the Pen. Each turn (click) of the Dose Knob dials 1 unit of insulin. You can give from 1 to 60 units in a single injection. If your dose is more than 60 units, you will need to give yourself more than 1 injection. The Plunger only moves a little with each injection, and you may not notice that it moves. The Plunger will only reach the end of the cartridge when you have used all 300 units in the Pen.

People who are blind or have vision problems should not use the Pen without help from a person trained to use the Pen.

How to recognize your HUMULIN N KwikPen

- Pen color: Beige
- Dose Knob: Light green
- Labels: White label with light green stripe

Supplies you will need to give your injection

- HUMULIN N KwikPen
- KwikPen compatible Needle (Becton, Dickinson and Company Pen Needles recommended)
- Alcohol swab
- Gauze

Preparing your Pen

- Wash your hands with soap and water.
- Check your Pen to make sure you are taking the right type of insulin. This is especially important if you use more than 1 type of insulin.
- Do not use your Pen past the expiration date printed on the Label or for more than 14 days after you first start using the Pen.
- Always use a new needle for each injection to help prevent infections and blocked needles. Do not reuse or share your needles with other people. You may give other people a serious infection or get a serious infection from them.

Step 1:

- Pull the Pen Cap straight off.
  - Do not remove the Pen Label.
- Wipe the Rubber Seal with an alcohol swab.
  - Do not attach the Needle before mixing.

Step 2:

- Gently roll the Pen between your hands 10 times.

Step 3:

- Move the Pen up and down (invert) 10 times.
  Mixing by rolling and inverting the Pen is important to make sure you get the right dose.

Step 4:

- Check the liquid in the Pen. HUMULIN N should look white and cloudy after mixing. Do not use if it looks clear or has any lumps or particles in it.

Step 5:

- Select a new Needle.
- Pull off the Paper Tab from the Outer Needle Shield.

Step 6:

- Push the capped Needle straight onto the Pen and twist the Needle on until it is tight.

Step 7:

- Pull off the Outer Needle Shield. Do not throw it away.
- Pull off the Inner Needle Shield and throw it away.

Priming your Pen

Prime before each injection.

- Priming your Pen means removing the air from the Needle and Cartridge that may collect during normal use and ensures that the Pen is working correctly.
- If you do not prime before each injection, you may get too much or too little insulin.

Step 8:

- To prime your Pen, turn the Dose Knob to select 2 units.

Step 9:

- Hold your Pen with the Needle pointing up. Tap the Cartridge Holder gently to collect air bubbles at the top.

Step 10:

- Continue holding your Pen with Needle pointing up. Push the Dose Knob in until it stops, and “0” is seen in the Dose Window. Hold the Dose Knob in and count to 5 slowly.
- You should see insulin at the tip of the Needle.
  - If you do not see insulin, repeat priming steps 8 to 10, no more than 4 times.
  - If you still do not see insulin, change the Needle and repeat priming steps 8 to 10.

Small air bubbles are normal and will not affect your dose.

Selecting your dose

- You can give from 1 to 60 units in a single injection.
- If your dose is more than 60 units, you will need to give more than 1 injection.
  - If you need help with dividing up your dose the right way, ask your healthcare provider.
  - Use a new Needle for each injection and repeat the priming step.

Step 11:

- Turn the Dose Knob to select the number of units you need to inject. The Dose Indicator should line up with your dose.
  - The Pen dials 1 unit at a time.
  - The Dose Knob clicks as you turn it.
  - Do not dial your dose by counting the clicks.You may dial the wrong dose. This may lead to you getting too much insulin or not enough insulin.
  - The dose can be corrected by turning the Dose Knob in either direction until the correct dose lines up with the Dose Indicator.
  - The even numbers (for example, 12) are printed on the dial.
  - The odd numbers, (for example, 25) after the number 1, are shown as full lines.
- Always check the number in the Dose Window to make sure you have dialed the correct dose.

(Example: 12 units shown in the Dose Window)
(Example: 25 units shown in the Dose Window)

- The Pen will not let you dial more than the number of units left in the Pen.
- If you need to inject more than the number of units left in the Pen, you may either:
  - inject the amount left in your Pen and then use a new Pen to give the rest of your dose,
  or
  - get a new Pen and inject the full dose.
- It is normal to see a small amount of insulin left in the Pen that you can not inject.

Giving your injection

- Inject your insulin as your healthcare provider has shown you.
- Change (rotate) your injection sites within the area you choose for each dose to reduce your risk of getting lipodystrophy (pits in skin or thickened skin) and localized cutaneous amyloidosis (skin with lumps) at the injection sites. Do not inject where the skin has pits, is thickened, or has lumps. Do not inject where the skin is tender, bruised, scaly or hard, or into scars or damaged skin.
- Do not try to change your dose while injecting.

Step 12:

- Choose your injection site.
  HUMULIN N is injected under the skin (subcutaneously) of your stomach area, buttocks, upper legs or upper arms.
- Wipe your skin with an alcohol swab, and let your skin dry before you inject your dose.

Step 13:

- Insert the Needle into your skin.
- Push the Dose Knob all the way in.
- Continue to hold the Dose Knob in and slowly count to 5 before removing the Needle.

Do not try to inject your insulin by turning the Dose Knob. You will not receive your insulin by turning the Dose Knob.

Step 14:

- Pull the Needle out of your skin.
  A drop of insulin at the Needle tip is normal. It will not affect your dose.
- Check the number in the Dose Window.
  - If you see “0” in the Dose Window, you have received the full amount you dialed.
  - If you do not see “0” in the Dose Window, do not redial. Insert the Needle into your skin and finish your injection.
  - If you still do not think you received the full amount you dialed for your injection, do not start over or repeat the injection. Monitor your blood glucose as instructed by your healthcare provider.
  - If you normally need to give 2 injections for your full dose, be sure to give your second injection.

The Plunger only moves a little with each injection, and you may not notice that it moves.
If you see blood after you take the Needle out of your skin, press the injection site lightly with a piece of gauze or an alcohol swab. Do not rub the area.

After your injection

Step 15:

- Carefully replace the Outer Needle Shield.

Step 16:

- Unscrew the capped Needle and throw it away (see Disposing of Pens and Needles section).
- Do not store the Pen with the Needle attached to prevent leaking, blocking the Needle, and air from entering the Pen.

Step 17:

- Replace the Pen Cap by lining up the Cap Clip with the Dose Indicator and pushing straight on.

Disposing of Pens and Needles

- Put your used needles in a FDA-cleared sharps disposal container right away after use. Do not throw away (dispose of) loose needles in your household trash.
- If you do not have a FDA-cleared sharps disposal container, you may use a household container that is:
  - made of a heavy-duty plastic,
  - can be closed with a tight-fitting, puncture-resistant lid, without sharps being able to come out,
  - upright and stable during use,
  - leak-resistant, and
  - properly labeled to warn of hazardous waste inside the container.
- When your sharps disposal container is almost full, you will need to follow your community guidelines for the right way to dispose of your sharps disposal container. There may be state or local laws about how you should throw away used needles and syringes. For more information about safe sharps disposal, and for specific information about sharps disposal in the state that you live in, go to the FDA's website at: http://www.fda.gov/safesharpsdisposal
- Do not dispose of your used sharps disposal container in your household trash unless your community guidelines permit this. Do not recycle your used sharps disposal container.
- The used Pen may be discarded in your household trash after you have removed the needle.

Storing your Pen

Unused Pens

- Store unused Pens in the refrigerator at 36°F to 46°F (2°C to 8°C).
- Do not freeze your insulin. Do not use if it has been frozen.
- Unused Pens may be used until the expiration date printed on the Label, if the Pen has been kept in the refrigerator.

In-use Pen

- Store the Pen you are currently using at room temperature [up to 86°F (30°C)]. Keep away from heat and light.
- Throw away the HUMULIN N Pen you are using after 14 days, even if it still has insulin left in it.

General information about the safe and effective use of your Pen

- Keep your Pen and needles out of the reach of children.
- Do not use your Pen if any part looks broken or damaged.
- Always carry an extra Pen in case yours is lost or damaged.

Troubleshooting

- If you can not remove the Pen Cap, gently twist the cap back and forth, and then pull the cap straight off.
- If the Dose Knob is hard to push:
  - Pushing the Dose Knob more slowly will make it easier to inject.
  - Your Needle may be blocked. Put on a new Needle and prime the Pen.
  - You may have dust, food, or liquid inside the Pen. Throw the Pen away and get a new Pen.

If you have any questions or problems with your HUMULIN N KwikPen, contact Lilly at 1-800-LillyRx (1-800-545-5979) or call your healthcare provider for help. For more information on HUMULIN N KwikPen and insulin, go to www.lilly.com.

Scan this code to launch

www.humulin.com

This Instructions for Use has been approved by the U.S. Food and Drug Administration.

HUMULIN® and HUMULIN® KwikPen® are trademarks of Eli Lilly and Company.

Revised: June 2022

Manufactured by:
Eli Lilly and Company
Indianapolis, IN 46285, USA
US License Number 1891

Copyright © 2013, 2022, Eli Lilly and Company. All rights reserved.

HUMULIN N KwikPen meets the current dose accuracy and functional requirements of ISO 11608-1.

LINNKP-0008-IFU-20220627

PACKAGE CARTON – HUMULIN N Vial 10 mL 1ct

NDC 0002-8315-01

100 units per mL (U-100)

Humulin® N

NPH

(insulin isophane human)

injectable suspension

10 mL multiple-dose vial

Use only with a U-100 syringe

For subcutaneous use only.

U-100

www.lilly.com

Lilly

PACKAGE LABEL – Humulin N KwikPen 3mL 5ct

5 x 3 mL prefilled pens

NDC 0002-8805-59

HP-8805

Humulin® N KwikPen®

NPH

(insulin isophane human)

injectable suspension

For Single Patient Use Only

Dispense in this sealed carton

Read Insulin Delivery Device Instructions for Use

For subcutaneous use only.

prefilled insulin delivery device

100 units per mL (U-100)

Needles not included

This device is suitable for use with Becton, Dickinson and Company's insulin pen needles.

Lilly